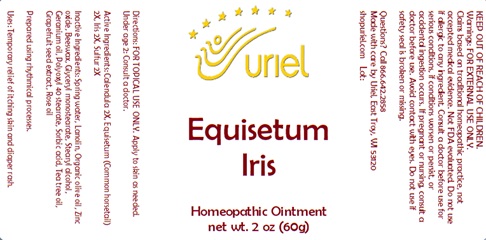 DRUG LABEL: Equisteum Iris
NDC: 48951-4129 | Form: OINTMENT
Manufacturer: Uriel Pharmacy Inc.
Category: homeopathic | Type: HUMAN OTC DRUG LABEL
Date: 20241212

ACTIVE INGREDIENTS: CALENDULA OFFICINALIS FLOWERING TOP 2 [hp_X]/1 g; EQUISETUM ARVENSE TOP 2 [hp_X]/1 g; C12-17 ALKANE 2 [hp_X]/1 g; SULFUR 2 [hp_X]/1 g
INACTIVE INGREDIENTS: WATER; LANOLIN; OLIVE OIL; ZINC OXIDE; YELLOW WAX; GLYCERYL MONOSTEARATE; STEARYL ALCOHOL; GERANIUM OIL, ALGERIAN TYPE; POLYOXYL 40 STEARATE; ROSE OIL; CITRUS PARADISI SEED; SORBIC ACID

Equisetum Iris

INDICATIONS AND USAGE

Directions: FOR TOPICAL USE ONLY.

DOSAGE AND ADMINISTRATION

Apply to skin as needed. Under age 2: Consult a doctor.

ACTIVE INGREDIENT

Active Ingredients: Calendula 2X, Equisetum (Common horsetail) 2X, Iris 2X, Sulfur 2X

INACTIVE INGREDIENT

Inactive Ingredients: Spring water, Lanolin, Organic olive oil, Zinc oxide, Beeswax, Glyceryl monostearate, Stearyl alcohol, Geranium oil, Polyoxyl 40 stearate, Sorbic acid, Tea tree oil, Grapefruit seed extract, Rose oil

Prepared using rhythmical processes.

PURPOSE

Uses: Temporary relief of itching skin and diaper rash.

KEEP OUT OF REACH OF CHILDREN.

Warnings: FOR EXTERNAL USE ONLY.
Claims based on traditional homeopathic practice, not accepted medical evidence. Not FDA evaluated. Do not use if allergic to any ingredient. Consult a doctor before use for serious conditions, if conditions worsen or persist, or accidental ingestion occurs. If pregnant or nursing consult a doctor before use. Avoid contact with eyes. Do not use if safety seal is broken or missing.

QUESTIONS

Questions? Call 866.642.2858 Made with care by Uriel, East Troy, WI 53120 shopuriel.com Lot: